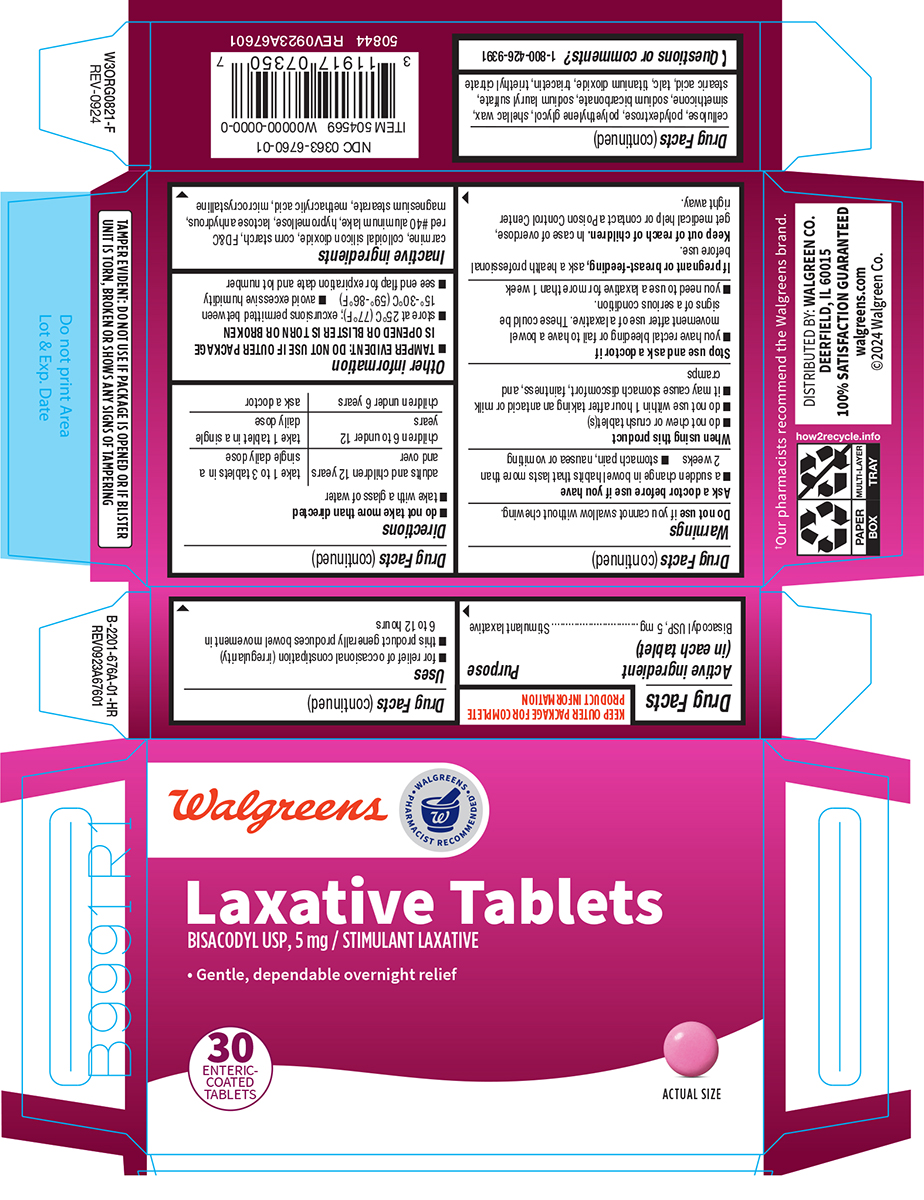 DRUG LABEL: Laxative
NDC: 0363-6760 | Form: TABLET, DELAYED RELEASE
Manufacturer: Walgreen Company
Category: otc | Type: HUMAN OTC DRUG LABEL
Date: 20260226

ACTIVE INGREDIENTS: BISACODYL 5 mg/1 1
INACTIVE INGREDIENTS: SILICON DIOXIDE; STARCH, CORN; FD&C RED NO. 40 ALUMINUM LAKE; HYPROMELLOSE, UNSPECIFIED; ANHYDROUS LACTOSE; MAGNESIUM STEARATE; METHACRYLIC ACID; MICROCRYSTALLINE CELLULOSE; POLYDEXTROSE; POLYETHYLENE GLYCOL, UNSPECIFIED; SHELLAC; DIMETHICONE; WATER; SODIUM BICARBONATE; SODIUM LAURYL SULFATE; STEARIC ACID; TALC; TITANIUM DIOXIDE; TRIACETIN; TRIETHYL CITRATE

Walgreens 44-676A

Active ingredient (in each tablet)

Bisacodyl USP, 5 mg

Purpose

Stimulant laxative

Uses

- for relief of occasional constipation (irregularity)
- this product generally produces bowel movement in 6 to 12 hours

Warnings

Do not use

if you cannot swallow without chewing.

Ask a doctor before use if you have

- a sudden change in bowel habits that lasts more than 2 weeks
- stomach pain, nausea or vomiting

When using this product

- do not chew or crush tablet(s)
- do not use within 1 hour after taking an antacid or milk
- it may cause stomach discomfort, faintness, and cramps

Stop use and ask a doctor if

- you have rectal bleeding or fail to have a bowel movement after use of a laxative. These could be signs of a serious condition.
- you need to use a laxative for more than 1 week

If pregnant or breast-feeding,

ask a health professional before use.

Keep out of reach of children.

In case of overdose, get medical help or contact a Poison Control Center right away.

Directions

- do not take more than directed
- take with a glass of water

adults and children 12 years and over | take 1 to 3 tablets in a single daily dose
children 6 to under 12 years | take 1 tablet in a single daily dose
children under 6 years | ask a doctor

Other information

- TAMPER EVIDENT: DO NOT USE IF OUTER PACKAGE IS OPENED OR BLISTER IS TORN OR BROKEN
- store at 25°C (77°F); excursions permitted between 15°-30°C (59°-86°F)
- avoid excessive humidity
- see end flap for expiration date and lot number

Inactive ingredients

carmine, colloidal silicon dioxide, corn starch, FD&C red #40 aluminum lake, hypromellose, lactose anhydrous, magnesium stearate, methacrylic acid, microcrystalline cellulose, polydextrose, polyethylene glycol, shellac wax, simethicone, sodium bicarbonate, sodium lauryl sulfate, stearic acid, talc, titanium dioxide, triacetin, triethyl citrate

Questions or comments?

1-800-426-9391

Principal display panel

Walgreens

Walgreens Pharmacist Recommended†

NDC 0363-6760-01

Laxative Tablets
BISACODYL USP, 5 mg / STIMULANT LAXATIVE

• Gentle, dependable overnight relief

30
ENTERIC -
COATED
TABLETS

ACTUAL SIZE

TAMPER EVIDENT: DO NOT USE IF PACKAGE IS OPENED OR IF BLISTER
UNIT IS TORN, BROKEN OR SHOWS ANY SIGNS OF TAMPERING

50844
REV0923A67601

†Our pharmacists recommend the Walgreens brand.

DISTRIBUTED BY: WALGREEN CO.
DEERFIELD, IL 60015
100% SATISFACTION GUARANTEED
walgreens.com
©2024 Walgreen Co.

Walgreens 44-676A